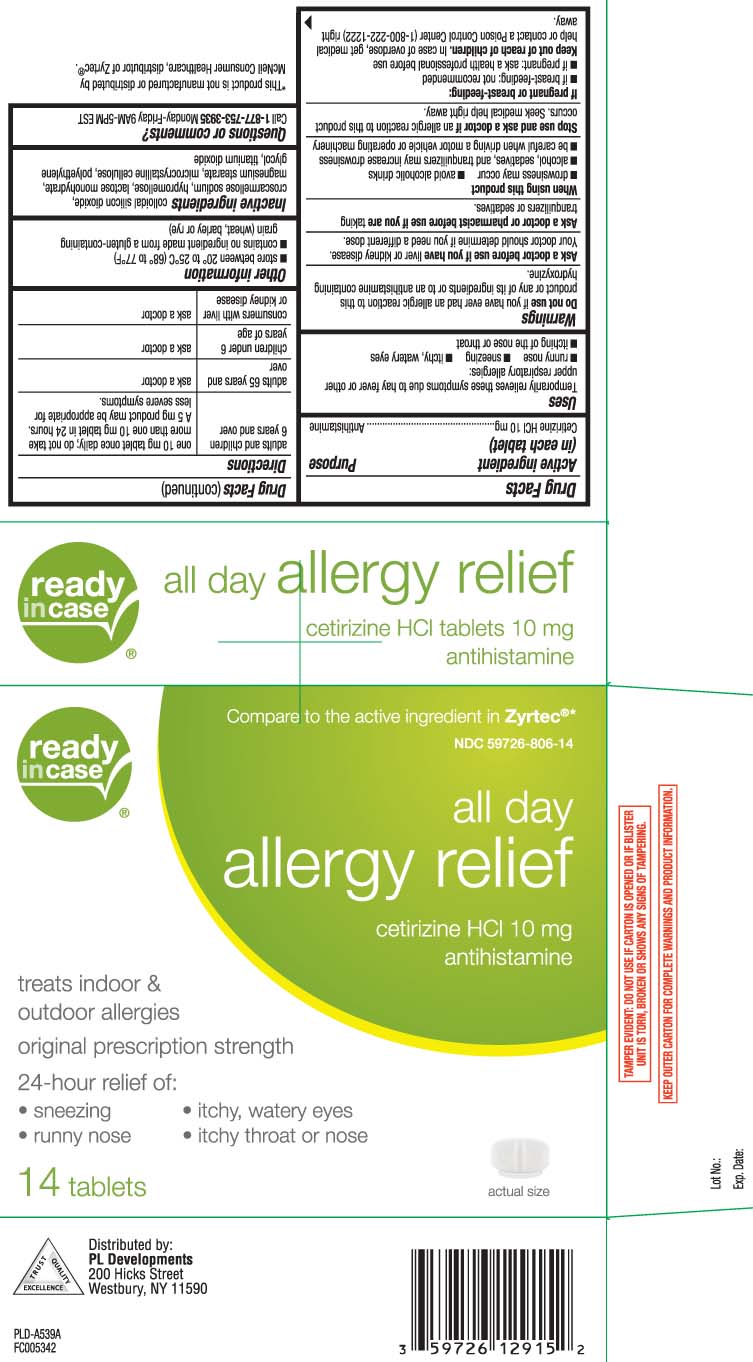 DRUG LABEL: All Day Allergy Relief
NDC: 59726-806 | Form: TABLET
Manufacturer: P & L Development, LLC
Category: otc | Type: HUMAN OTC DRUG LABEL
Date: 20260223

ACTIVE INGREDIENTS: CETIRIZINE HYDROCHLORIDE 10 mg/1 1
INACTIVE INGREDIENTS: LACTOSE MONOHYDRATE; MAGNESIUM STEARATE; POLYETHYLENE GLYCOL, UNSPECIFIED; SILICON DIOXIDE; CROSCARMELLOSE SODIUM; HYPROMELLOSE, UNSPECIFIED; TITANIUM DIOXIDE; MICROCRYSTALLINE CELLULOSE

Drug Facts

Active ingredient (in each tablet)

Cetirizine HCl 10 mg

Purpose

Antihistamine

Uses

- temporarily relieves these symptoms due to hay fever or other upper respiratory allergies:
  - runny nose
  - sneezing
  - itchy, watery eyes
  - itching of the nose or throat

Warnings

Do not use

if you have ever had an allergic reaction to this product or any of its ingredients or to an antihistamine containing hydroxyzine.

Ask a doctor before use if you have

liver or kidney disease. Your doctor should determine if you need a different dose.

Ask a doctor or pharmacist before use if you are

taking tranquilizers or sedatives.

When using this product

- drowsiness may occur
- alcohol, sedatives, and tranquilizers may increase drowsiness
- avoid alcoholic drinks
- be careful when driving a motor vehicle or operating machinery

Stop use and ask a doctor if

an allergic reaction to this product occurs. Seek medical help right away.

If pregnant or breast-feeding:

- if breast-feeding: not recommended
- if pregnant: ask a health professional before use

Keep out of reach of children.

In case of overdose, get medical help or contact a Poison Control Center (1-800-222-1222) right away.

Directions

adults and children 6 years and over | Take one 10 mg tablet once daily; do not take more than one 10 mg tablet in 24 hours. A 5 mg product may be appropriate for less severe symptoms.
adults 65 years and over | ask a doctor
children under 6 years of age | ask a doctor
consumers with liver or kidney disease | ask a doctor

Other Information

- store between 20º to 25ºC (68º to 77ºF)
- contains no ingredient made from a gluten-containing grain(wheat, barley or rye)

Inactive ingredients

colloidal silicon dioxide, croscarmellose sodium, hypromellose, lactose monohydrate, magnesium stearate, microcrystalline cellulose, polyethylene glycol, titanium dioxide

Questions or comments?

Call 1-877-753-3935 Monday-Friday 9AM-5PM EST

Principal Display Panel

Compare to the active ingredient in Zyrtec®*

all day allergy relief

cetirizine HCl 10 mg

antihistamine

treats indoor & outdoor allergies

original prescription strength

24 hour relief of:

- sneezing
- itchy, watery eyes
- runny nose
- itchy throat or nose

tablets

*This product is not manufactured or distributed by McNeil Consumer Healthcare, distributor of Zyrtec®.

TAMPER EVIDENT: DO NOT USE IF CARTON IS OPENED OR IF BLISTER UNIT IS TORN, BROKEN OR SHOWS ANY SIGNS OF TAMPERING.

KEEP OUTER CARTON FOR COMPLETE WARNINGS AND PRODUCT INFORMATION.

Distributed by:

PL Developments

200 Hicks Street

Westbury, NY 11590

Package Labeling

READYinCASE All Day Allergy Relief